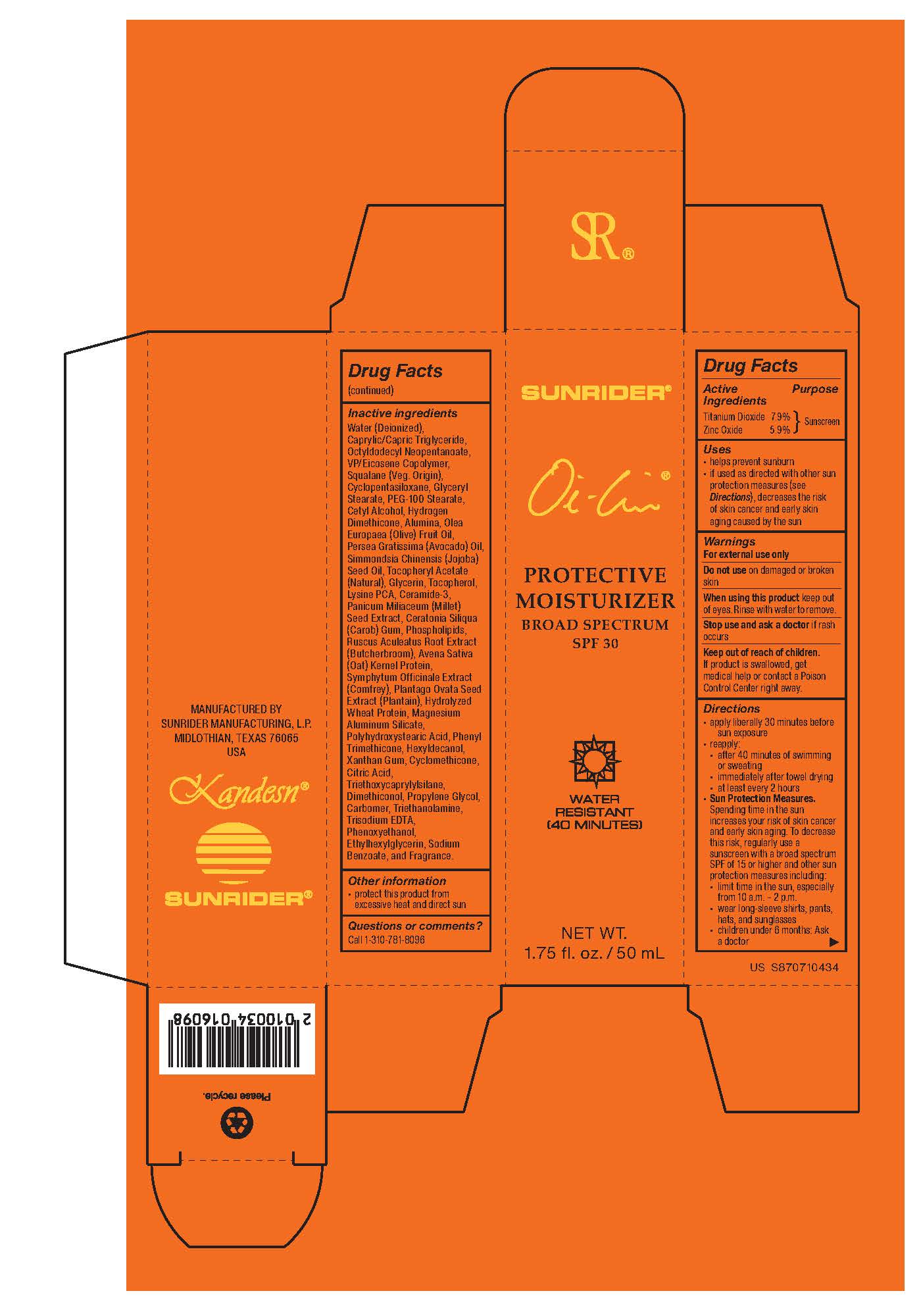 DRUG LABEL: Oi-Lin Protective Moisturizer Broad Spectrum SPF 30
NDC: 62191-100 | Form: CREAM
Manufacturer: Sunrider Manufacturing L.P.
Category: otc | Type: HUMAN OTC DRUG LABEL
Date: 20251230

ACTIVE INGREDIENTS: TITANIUM DIOXIDE 114 mg/1 g; ZINC OXIDE 55 mg/1 g
INACTIVE INGREDIENTS: CARBOMER; TRIETHANOLAMINE; SODIUM BENZOATE; CYCLOPENTASILOXANE; OCTYLDODECYL NEOPENTANOATE; VINYLPYRROLIDONE/EICOSENE COPOLYMER; GLYCERYL STEARATE; PEG-100 STEARATE; CETYL ALCOHOL; OLEA EUROPAEA (OLIVE) FRUIT OIL; SIMMONDSIA CHINENSIS (JOJOBA) SEED OIL; MILLET; RUSCUS ACULEATUS ROOT; COMFREY; PLANTAGO OVATA SEED; HYDROLYZED WHEAT PROTEIN (ENZYMATIC, 3000 MW); POLYHYDROXYSTEARIC ACID (2300 MW); HEXYLDECANOL; XANTHAN GUM; DIMETHICONOL (40 CST); TRISODIUM EDTA; PHENOXYETHANOL; ETHYLHEXYLGLYCERIN; CAPRYLIC/CAPRIC TRIGLYCERIDE; HYDROGEN DIMETHICONE (20 CST); ALUMINA; PERSEA GRATISSIMA (AVOCADO) OIL; .ALPHA.-TOCOPHEROL ACETATE; .DELTA.-TOCOPHEROL; EGG PHOSPHOLIPIDS; MAGNESIUM ALUMINUM SILICATE; OATMEAL; CITRIC ACID; SQUALANE; CAROB; TRIETHOXYCAPRYLYLSILANE; WATER; DIGLYCERIN; LYSINE PCA; CERAMIDE 3; PHENYL TRIMETHICONE; CYCLOMETHICONE

Active ingredients:

Titanium Dioxide 7.9 %

Zinc Oxide 5.9 %

PURPOSE

Sunscreen

- helps prevent sunburn
- if used as direct with other sun protection measures, decreases the risk of skin cancer and early skin aging caused by the sun

Warnings:

For external use only.

Do not use on damaged or broken skin.

When using this product keep out of eyes. Rinse with water to remove.

Stop use end ask a doctor if rash occurs.

Keep out of reach of children.

If product is swallowed, get medical help or contact a Poison Control Center

right away.

INACTIVE INGREDIENT

Water (Deionized)

Caprylic/Capric Triglyceride

Octyldodecyl Neopentanoate

VP/Eicosene Copolymer

Squalane (Veg. Origin)

Cyclopentasiloxane

Glyceryl Stearate

PEG-100 Stearate

Cetyl Alcohol

Hydrogen Dimethicone

Alumina

Olea Europaea (Olive) Fruit Oil

Persea Gratissima (Avocado) Oil

Simmondsia Chinensis (Jojoba) Seed Oil

Tocopheryl Acetate (Natural)

Glycerin

Tocopherol

Lysine PCA

Ceramide-3

Panicum Miliaceum (Millet) Seed Extract

Ceratonia Siliqua (Carob) Gum

Phospholipids

Ruscus Aculeatus Root Extract (Butcherbroom)

Avena Sativa (Oat) Kernel Protein

Symphytum Officinale Extract (Comfrey)

Plantago Ovata Seed Extract (Plantain)

Hydrolyzed Wheat Protein

Magnesium Aluminum Silicate

Polyhydroxystearic Acid

Phenyl Trimethicone

Hexyldecanol

Xanthan Gum

Cyclomethicone

Citric Acid

Triethoxycaprylylsilane

Dimethiconol

Propylene Glycol

Carbomer

Triethanolamine

Trisodium EDTA

Phenoxyethanol

Ethylhexylglycerin

Sodium Benzoate

Fragrance

Keep out of reach of children.

If product is swallowed, get medical help or contact a Poison Control Center

right away.

WARNINGS AND PRECAUTIONS

Sun Protection Measures

Spending time in the sun increases your risk of skin cancer and early skin aging. To decrease this risk,

regularly use a sunscreen with a broad-spectrum SPF of 15 or higher and other sun protection measures

including:

- limit time in the sun, especially from10 a.m. – 2 p.m.
- wear long sleeve shirts, pants, hats, and sunglasses,
- children under 6 months: Ask a doctor.

Directions:

Apply liberally 30 minutes before sun exposure.

Reapply:

- after 40 minutes of swimming or sweating,
- immediately after towel drying,
- at least every 2 hours.

Directions:

Apply liberally 15 minutes before sun exposure

Reapply:

- after 40 minutes of swimming or sweating,
- immediately after towel drying,
- at least every 2 hours.